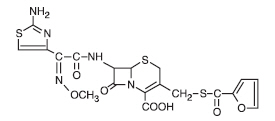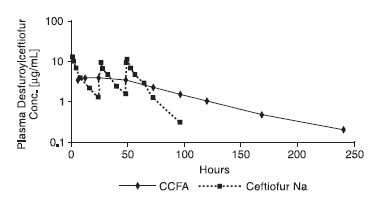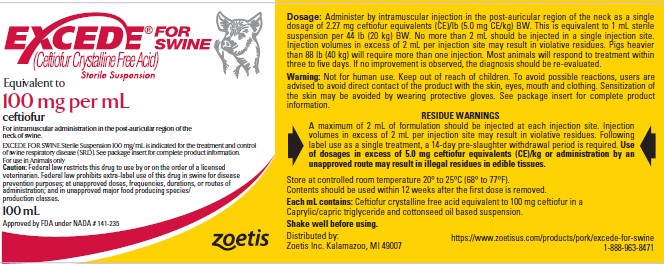 DRUG LABEL: Excede for Swine
NDC: 54771-5223 | Form: INJECTION, SUSPENSION
Manufacturer: Zoetis Inc.
Category: animal | Type: PRESCRIPTION ANIMAL DRUG LABEL
Date: 20250808

ACTIVE INGREDIENTS: CEFTIOFUR 100 mg/1 mL

EXCEDE®
For Swine (Ceftiofur Crystalline Free Acid)
Sterile Suspension, 100 mg/mL

FOR
SWINE

For intramuscular administration in the post-auricular region of the neck of swine.

CAUTION

Federal law restricts this drug to use by or on the order of a licensed veterinarian. Fed eral law prohibits extra-label use of this drug in swine for disease prevention purposes; at unapproved doses, frequencies, durations, or routes of administration; and in unap proved major food producing species/ pro duction classes.

DESCRIPTION

EXCEDE FOR SWINE Sterile Suspension 100 mg/mL is a ready-to-use formulation that contains the crystalline free acid of ceftiofur, which is a broad spectrum cephalosporin antibiotic active against gram-positive and gram-negative bacteria including ß-lactamase-producing strains. Like other cephalosporins, ceftiofur is bactericidal in vitro, resulting from inhibition of cell wall synthesis.

Each mL of this ready-to-use sterile suspension contains ceftiofur crystalline free acid equivalent to 100 mg ceftiofur, in a Caprylic/capric triglyceride and cottonseed oil based suspension.

Figure 1. Structure of ceftiofur crystalline free acid:

Chemical name of ceftiofur crystalline free acid:

7-[[2-(2-Amino-4-thiazolyl)-2-(methoxyimino)acetyl]amino]-3-[[(2-furanylcarbonyl)thio]methyl]-8-oxo-5-thia-1-azabicyclo[4.2.0]oct-2-ene 2-carboxylic acid

INDICATIONS

EXCEDE FOR SWINE Sterile Suspension 100 mg/mL is indicated for the treatment of swine respiratory disease (SRD) associated with Actinobacillus pleuropneumoniae, Pasteurella multocida, Haemophilus parasuis, and Streptococcus suis; and for the control of SRD associated with Actinobacillus pleuropneumoniae, Pasteurella multocida, Haemophilus parasuis, and Streptococcus suis in groups of pigs where SRD has been diagnosed.

DOSAGE AND ADMINISTRATION

DOSAGE

Administer by intramuscular (IM) injection in the post-auricular region of the neck as a single dosage of 2.27 mg ceftiofur equivalents (CE)/lb (5.0 mg CE/kg) body weight (BW). This is equivalent to 1 mL sterile suspension per 44 lb (20 kg) BW. No more than 2 mL should be injected in a single injection site. Injection volumes in excess of 2 mL per injection site may result in violative residues. Pigs heavier than 88 lb (40 kg) will require more than one injection.

Most animals will respond to treatment within three to five days. If no improvement is observed, the diagnosis should be re-evaluated.

ADMINISTRATION

Shake well before using. EXCEDE FOR SWINE Sterile Suspension 100 mg/mL is to be administered by intramuscular injection in the post-auricular region of the neck.

CONTRAINDICATIONS

As with all drugs, the use of EXCEDE FOR SWINE Sterile Suspension 100 mg/mL is contraindicated in animals previously found to be hypersensitive to the drug.

WARNINGS

FOR USE IN ANIMALS ONLY. NOT FOR HUMAN USE. KEEP OUT OF REACH OF CHILDREN.

Penicillins and cephalosporins can cause allergic reactions in sensitized individuals. Topical exposures to such antimicrobials, including ceftiofur, may elicit mild to severe allergic reactions in some individuals. Repeated or prolonged exposure may lead to sensitization. Avoid direct contact of the product with the skin, eyes, mouth and clothing. Sensitization of the skin may be avoided by wearing protective gloves.

Persons with a known hypersensitivity to penicillin or cephalosporins should avoid exposure to this product.

In case of accidental eye exposure, flush with water for 15 minutes. In case of accidental skin exposure, wash with soap and water. Remove contaminated clothing. If allergic reaction occurs (e.g., skin rash, hives, difficult breathing), seek medical attention.

The material safety data sheet contains more detailed occupational safety information. To report adverse effects in users, to obtain more information or to obtain a material safety data sheet, call 1-888-963-8471.

RESIDUE WARNINGS

- A maximum of 2 mL of formulation should be injected at each injection site. Injection volumes in excess of 2 mL per injection site may result in violative residues.
- Following label use as a single treatment, a 14-day pre-slaughter withdrawal period is required.
- Use of dosages in excess of 5.0 mg ceftiofur equivalents (CE)/kg or administration by an unapproved route may result in illegal residues in edible tissues.

PRECAUTIONS

The safety of ceftiofur has not been demonstrated for pregnant swine or swine intended for breeding.

Administration of EXCEDE FOR SWINE Sterile Suspension 100 mg/mL as directed may induce a transient reaction at the site of injection and underlying tissues that may result in trim loss of edible tissue at slaughter.

ADVERSE REACTIONS

An injection site tolerance study demonstrated that EXCEDE FOR SWINE Sterile Suspension 100 mg/mL is well tolerated in pigs. Half of the injection sites at both 3 and 7 days post-injection were scored as "negative" for irritation and the other half were scored as "slight irritation". All gross observations and measurements of injection sites qualified the sites at 10 days post-injection as "negative" for irritation.

No adverse effects were observed in multi-location field efficacy studies involving more than 1000 pigs.

CLINICAL PHARMACOLOGY

Ceftiofur administered as either ceftiofur sodium (NAXCEL® Sterile Powder), ceftiofur hydrochloride (EXCENEL® RTU Sterile Suspension) or ceftiofur crystalline free acid (EXCEDE FOR SWINE Sterile Suspension 100 mg/mL) is metabolized rapidly to desfuroylceftiofur, the primary metabolite. Administration of ceftiofur to swine as ceftiofur crystalline free acid (CCFA) at a single IM dosage of 2.27 mg CE/lb (5.0 mg CE/kg) BW provides concentrations of ceftiofur and desfuroylceftiofurrelated metabolites in plasma that are multiples above the MIC90 [Minimum inhibitory concentration for 90% of the isolates] for the SRD label pathogens Actinobacillus pleuropneumoniae, Pasteurella multocida, Haemophilus parasuis and Streptococcus suis for an extended period of time (see Figure 2 and Tables 1–2).

The average plasma concentrations of ceftiofur- and desfuroylceftiofur-related metabolites for CCFA (EXCEDE FOR SWINE Sterile Suspension 100 mg/mL) after IM administration of 2.27 mg CE/lb (5.0 mg CE/kg) BW and those for ceftiofur sodium (NAXCEL Sterile Powder) after IM administration at 1.36 mg CE/lb (3 mg CE/kg) BW for three consecutive days are presented in Figure 2 below.

Figure 2. Average plasma concentrations of ceftiofur- and desfuroylceftiofur-related metabolites for CCFA (EXCEDE FOR SWINE Sterile Suspension 100 mg/mL) after IM administration of 2.27 mg CE/lb (5.0 mg CE/kg) BW and those for ceftiofur sodium (NAXCEL Sterile Powder) after IM administration at 1.36 mg CE/lb (3 mg CE/kg) BW for three consecutive days

Pharmacokinetic parameters measured after a single IM administration of 2.27 mg CE/lb (5.0 mg CE/kg) BW of EXCEDE FOR SWINE Sterile Suspension 100 mg/mL in the post-auricular region of the neck of swine are presented in the following table (Table 1).

Table 1. Pharmacokinetic parameters in swine after a single IM administration of EXCEDE FOR SWINE Sterile Suspension 100 mg/mL at 2.27 mg CE/lb (5.0 mg CE/kg) BW
Pharmacokinetic Parameter | Mean Value ± Standard Deviation (non-compartmental analyses)
Cmax (μg/mL) | 4.17 ± 0.92
tmax (h) | 22.0 ± 12.2
AUC 0-LOQ (μg∙h/mL) | 373.0 ± 56.1
t1/2 (h) | 49.6 ± 11.8
Cmax = maximum plasma concentration (in μg CE/mL)
tmax = the time after injection when Cmax occurs (in hours)
AUC 0-LOQ = the area under the plasma concentration vs. time curve from time of injection to the limit of quantitation of the assay (0.15 μg CE/mL)
t1/2 = terminal phase biological half-life (in hours)

Table 2. Ceftiofur minimum inhibitory concentration (MIC) values [The correlation between in vitro susceptibility data and clinical effectiveness is unknown.] of indicated pathogens isolated from SRD treatment and control field studies conducted in the U.S.
Indicated Pathogens | Year(s) of Isolation | Field Study | Number of Isolates | MIC50 [The lowest MIC to encompass 50% and 90% of the most susceptible isolates, respectively.] (μg/mL) | MIC90 (μg/mL) | MIC Range (μg/mL)
Actinobacillus pleuropneumoniae | 2000 to 2001 | Treatment | 5 | NA | NA | ≤0.03 to 0.06
Actinobacillus pleuropneumoniae | 2009 | Control | 34 | 0.03 | 0.06 | 0.015 to 0.06
Pasteurella multocida | 2000 to 2001 | Treatment | 20 | ≤0.03 | ≤0.03 | ≤0.03 [No range; all isolates yielded the same value.]
Pasteurella multocida | 2009 | Control | 67 | ≤0.004 | ≤0.004 | ≤0.004
Streptococcus suis | 2000 to 2001 | Treatment | 30 | 0.06 | 0.12 | ≤ 0.03 to 0.5
Streptococcus suis | 2009 | Control | 141 | 0.25 | 1 | 0.03 to >2

MICROBIOLOGY

Ceftiofur has demonstrated in vitro activity against Actinobacillus pleuropneumoniae, Pasteurella multocida, Haemophilus parasuis, and Streptococcus suis, four major pathogenic bacteria associated with SRD.

The minimum inhibitory concentrations (MICs) of ceftiofur against indicated SRD pathogens were determined using methods recommended by the Clinical and Laboratory Standards Institute (CLSI) using the M31-A and M31-A3 standards for the SRD treatment (2000-2001) and control (2009) studies, respectively. Isolates from the SRD treatment study were obtained from lung tissue collected from non-treated pigs prior to enrollment and saline-treated pigs that died or were euthanized during the study. Isolates from the SRD control study were obtained from lung tissue from non-treated pigs euthanized prior to enrollment and from saline- and ceftiofur-treated pigs that died or were euthanized during the study. The susceptibility results for the treatment and control studies are presented in Table 2.

Based on pharmacokinetic data from studies of ceftiofur in swine after a single intramuscular injection of 2.27 mg CE/lb (5.0 mg CE/kg) BW, the following interpretive criteria are recommended by CLSI:

Table 3. CLSI-accepted interpretive criteria for ceftiofur against swine respiratory disease pathogens [These interpretive criteria should only be used when the CLSI M31-A3 performance standard is used to determine antimicrobial susceptibility to ceftiofur.]
Pathogens | Disk Potency | Zone Diameter (mm) | MIC (μg/mL) | Interpretation
Actinobacillus pleuropneumoniae Pasteurella multocida Streptococcus suis | 30 μg | ≥21 | ≤2.0 | (S) Susceptible
Actinobacillus pleuropneumoniae Pasteurella multocida Streptococcus suis | 30 μg | 18-20 | 4.0 | (I) Intermediate
Actinobacillus pleuropneumoniae Pasteurella multocida Streptococcus suis | 30 μg | ≤17 | ≥8.0 | (R) Resistant

EFFECTIVENESS

The effectiveness of a single dose of 2.27 or 3.18 mg CE/lb BW (5.0 or 7.0 mg CE/kg BW) EXCEDE FOR SWINE Sterile Suspension 100 mg/mL for the treatment of SRD was confirmed in a well-controlled, multi-location field study. A total of 706 pigs with clinical signs of bacterial respiratory disease were enrolled and treated with a placebo injection or EXCEDE FOR SWINE Sterile Suspension 100 mg/mL administered as a single IM injection in the post-auricular region of the neck. Clinical observations were performed on Days 1-7 and rectal temperatures were taken on Days 1, 3, and 6 following treatment (Day 0). Necropsies were performed on all pigs that died during the study and after euthanasia of all remaining study pigs at the end of the 14-day post-enrollment study period. Lung lesions were scored and lungs were submitted for bacterial identification. Mortality rates were numerically lower (but not statistically different) for the EXCEDE FOR SWINE Sterile Suspension 100 mg/mL-treated groups (4.3% for the 5.0 mg CE/kg BW group and 4.2% for the 7.0 mg CE/kg BW group) compared with the placebo-treated control group (6.3%). There was a statistically significant (p<0.05) improvement in clinical cure rates for the EXCEDE FOR SWINE Sterile Suspension 100 mg/mL-treated groups (24.8% for the 5.0 mg CE/kg BW group and 26.4% for the 7.0 mg CE/kg BW group) compared with the placebo-treated control group (17.7%). Lung lesion scores were numerically higher (but not statistically different) for the EXCEDE FOR SWINE Sterile Suspension 100 mg/mL-treated groups (10.4% for both the 5.0 mg CE/kg BW and the 7.0 mg CE/kg BW group) compared with the placebo-treated control group (9.2%). Bacteriological culture of the lungs of study pigs identified the following respiratory pathogens: Actinobacillus pleuropneumoniae, Pasteurella multocida, Haemophilus parasuis, and Streptococcus suis.

The effectiveness of a single dose of 2.27 CE/lb BW (5.0 mg CE/kg BW) EXCEDE FOR SWINE for the control of SRD was evaluated in a multi-location natural infection field study. At each site, when at least 15% of the study candidates in a pen showed clinical signs of SRD, all pigs in the pen were enrolled and treated with EXCEDE FOR SWINE (n = 346) or saline (n = 347). Responses to treatment were evaluated 7 days post-treatment. Success was defined as a pig that survived to Day 7 and had normal attitude, normal respiration, and a rectal temperature of < 104 °F. The treatment success rate was significantly higher (p = 0.0188) for EXCEDE FOR SWINE-treated pigs (59.6%) compared to the saline-treated pigs (41.4%). Bacteriological culture of the lungs of study pigs identified the following respiratory pathogens: Actinobacillus pleuropneumoniae, Pasteurella multocida, Haemophilus parasuis, and Streptococcus suis.

ANIMAL SAFETY

After parenteral administration, CCFA, ceftiofur sodium, and ceftiofur hydrochloride are metabolized to the same principal metabolite, desfuroylceftiofur. Plasma levels achieved are similar after recommended dosing (Figure 2). Therefore, studies conducted with ceftiofur sodium are adequate to evaluate the systemic safety of CCFA. Results from a five-day tolerance study in normal feeder pigs indicated that ceftiofur sodium produced no overt adverse signs of toxicity and was well tolerated when administered at 57 mg CE/lb (125 mg/kg) BW (more than 25 times the recommended dosage of CCFA) for five consecutive days.

Table 4. Acceptable quality control ranges for ceftiofur against CLSI recommended American Type Culture Collection (ATCC) reference strains
Organism Name (ATCC No.) | MIC (μg/mL) | Zone Diameter, mm (Disk Content 30 μg)
E. coli ATCC 25922 | 0.25–1.0 | 26–31
S. aureus ATCC 29213 | 0.25–1.0 | —
S. aureus ATCC 25923 | — | 27–31
P. aeruginosa ATCC 27853 | 16.0–64.0 | 14–18

An additional dose toxicity study was conducted to determine the safety margin of ceftiofur in swine. Five barrows and five gilts per group were administered ceftiofur sodium IM at 0, 2.27, 6.81 and 11.36 mg CE/lb (0, 5, 15, 25 mg CE/kg) BW (0, 1, 3 and 5 times the recommended dosage for CCFA) for 15 consecutive days. There were no adverse systemic effects observed, indicating that ceftiofur sodium has a wide margin of safety when administered intramuscularly in feeder pigs.

A separate study evaluated the injection site tissue tolerance of EXCEDE FOR SWINE Sterile Suspension 100 mg/mL in swine when administered intramuscularly as a single injection at the maximum recommended dose volume of 2 mL (approximately 5 mg CE/kg BW) per injection site. Because injection site volumes greater than 2 mL may result in violative residues, only injection volumes of 2 mL were evaluated in this study. EXCEDE FOR SWINE Sterile Suspension 100 mg/mL was injected intramuscularly into each side of the neck of six swine at a dose volume of 2 mL/injection site. Clinical observations were made daily. At 3, 7 and 10 days post-injection, pairs of animals were euthanized and the neck injection sites were dissected for pathological examination (4 injection sites per time point). The injections were well tolerated in all pigs. Clinically, injection site reactions ranged from nondetectable (6 of 12 sites) to a transitory (up to 4 days post-injection) palpable, nonvisible swelling (2 of 12 sites) or a small, visible, reddened nodule at the needle insertion point (4 of 12 sites; 3 of 4 nodules were barely detectable by 3 to 7 days post-injection). There was no clinical evidence of the injections at 10 days post-injection. At necropsy, half of the injection sites at both 3 and 7 days post-injection were scored as "negative" for irritation and the other half were scored as "slight irritation". One animal had a visible lesion described as an area of tan with red speckles present in the deep muscle fascia, less than 6 cm2, at 10 days post-injection; this lesion and the remaining injection sites evaluated at 10 days post-injection were scored as "negative" for irritation.

STORAGE CONDITIONS

Store at controlled room temperature 20° to 25°C (68° to 77°F). Shake well before using. Contents should be used within 12 weeks after the first dose is removed.

HOW SUPPLIED

EXCEDE FOR SWINE Sterile Suspension 100 mg/mL is available in the following package size:

100 mL vial

Approved by FDA under NADA # 141-235
zoetis
Distributed by:
Zoetis Inc.Kalamazoo, MI 49007

https://www.zoetisus.com/products/pork/excede-for-swine or call
1-888-963-8471
Revised: March 2025
40052847

PRINCIPAL DISPLAY PANEL - 100 mL Vial Label

100 mL Vial Label

40052845